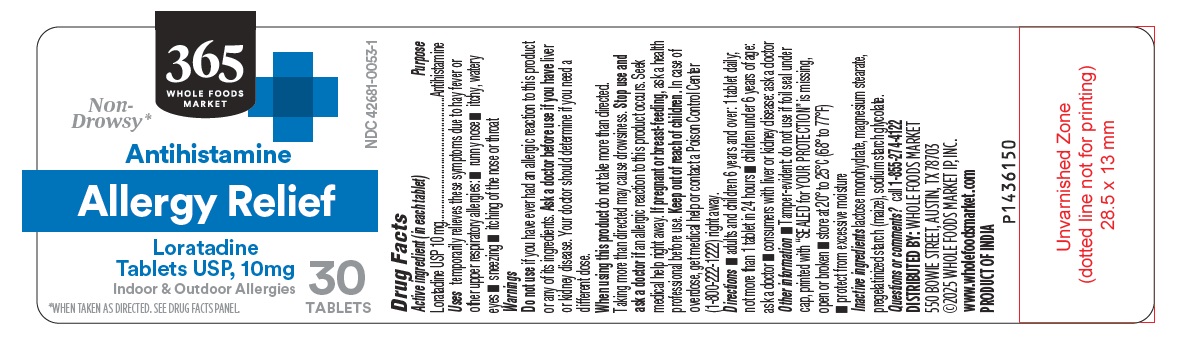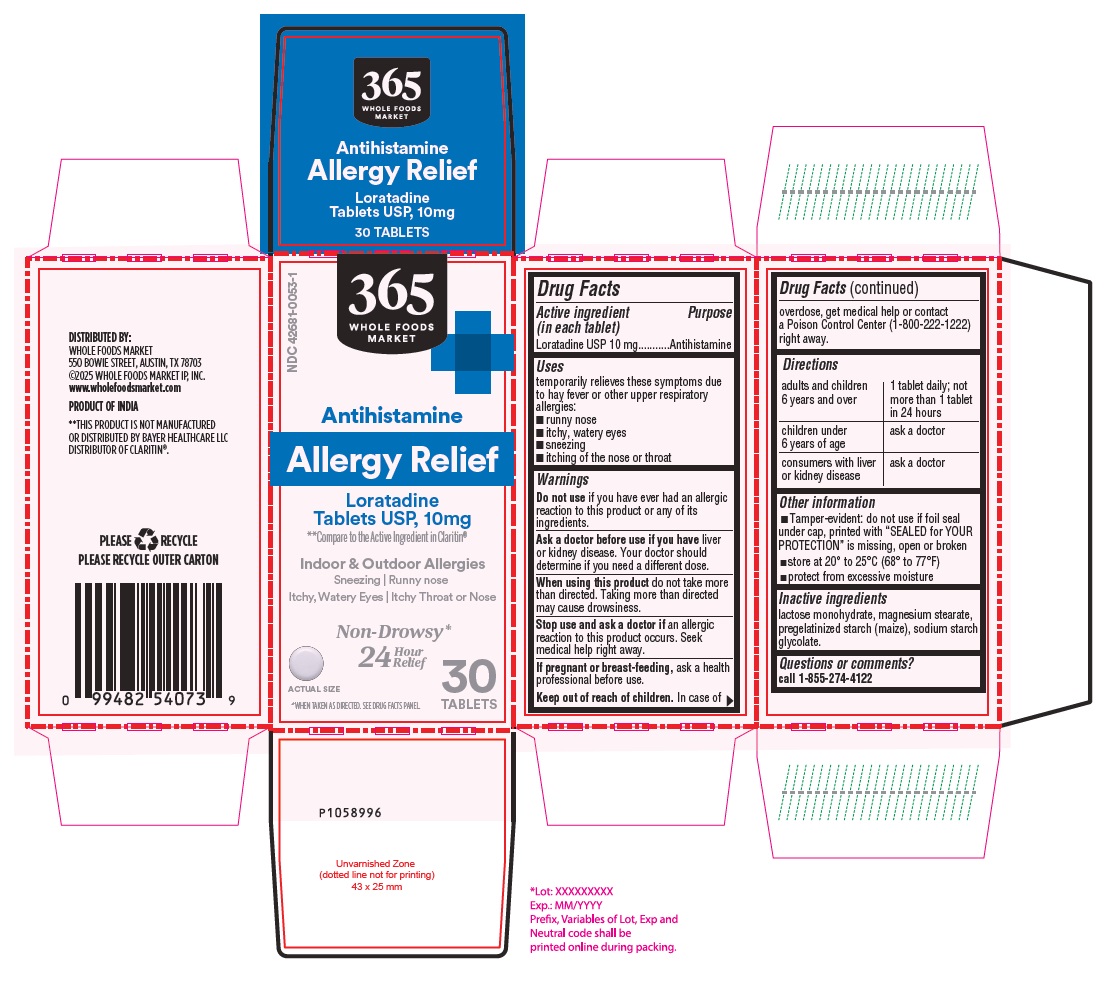 DRUG LABEL: 365 Whole Foods Market Loratadine
NDC: 42681-0053 | Form: TABLET
Manufacturer: Whole Foods Market, Inc.
Category: otc | Type: Human OTC Drug Label
Date: 20250611

ACTIVE INGREDIENTS: LORATADINE 10 mg/1 1
INACTIVE INGREDIENTS: LACTOSE MONOHYDRATE; MAGNESIUM STEARATE; STARCH, CORN; SODIUM STARCH GLYCOLATE TYPE A POTATO

Loratadine Tablets USP 10 mg

Active ingredient (in each tablet)

Loratadine USP 10 mg

Purpose

Antihistamine

Uses

temporarily relieves these symptoms due to hay fever or other upper respiratory allergies:

- runny nose
- itchy, watery eyes
- sneezing
- itching of the nose or throat

Warnings

Do not use
if you have ever had an allergic reaction to this product or any of its ingredients.

Ask a doctor before use if you have

liver or kidney disease. Your doctor should determine if you need a different dose.

When using this product

do not take more than directed. Taking more than directed may cause drowsiness.

Stop use and ask a doctor if

an allergic reaction to this product occurs. Seek medical help right away.

If pregnant or breast-feeding,

ask a health professional before use.

Keep out of reach of children.

In case of overdose, get medical help or contact a Poison Control Center (1-800-222-1222) right away.

Directions

adults and children 6 years and over | 1 tablet daily; not more than 1 tablet in 24 hours
children under 6 years of age | ask a doctor
consumers with liver or kidney disease | ask a doctor

Other information

- Tamper-evident: do not use if foil seal under cap, printed with “SEALED for YOUR PROTECTION” is missing, open or broken
- store at 20° to 25°C (68° to 77°F)
- protect from excessive moisture

Inactive ingredients

lactose monohydrate, magnesium stearate, pregelatinized starch (maize), sodium starch glycolate.

Questions or comments?

call 1-855-274-4122

DISTRIBUTED BY:

WHOLE FOODS MARKET

550 BOWIE STREET, AUSTIN, TX 78703

©2025 WHOLE FOODS MARKET IP, INC.

www.wholefoodsmarket.com

PRODUCT OF INDIA

PACKAGE LABEL-PRINCIPAL DISPLAY PANEL - 10 mg (30 Tablets Container Label)

365

WHOLE FOODS

MARKET

NDC 42681-0053-1

Non-

Drowsy*

Antihistamine

Allergy Relief

Loratadine
Tablets USP, 10mg

Indoor & Outdoor Allergies
*WHEN TAKEN AS DIRECTED. SEE DRUG FACTS PANEL.

30

TABLETS

PACKAGE LABEL-PRINCIPAL DISPLAY PANEL - 10 mg (30 Tablets Container Carton)

NDC 42681-0053-1

365

WHOLE FOODS

MARKET

Antihistamine
Allergy Relief
Loratadine
Tablets USP, 10mg

**Compare to the Active Ingredient in Claritin®

Indoor & Outdoor Allergies

Sneezing | Runny nose

Itchy, Watery Eyes | Itchy Throat or Nose

Non-Drowsy*

24 Hour

Relief

ACTUAL SIZE

*WHEN TAKEN AS DIRECTED. SEE DRUG FACTS PANEL.

30

TABLETS